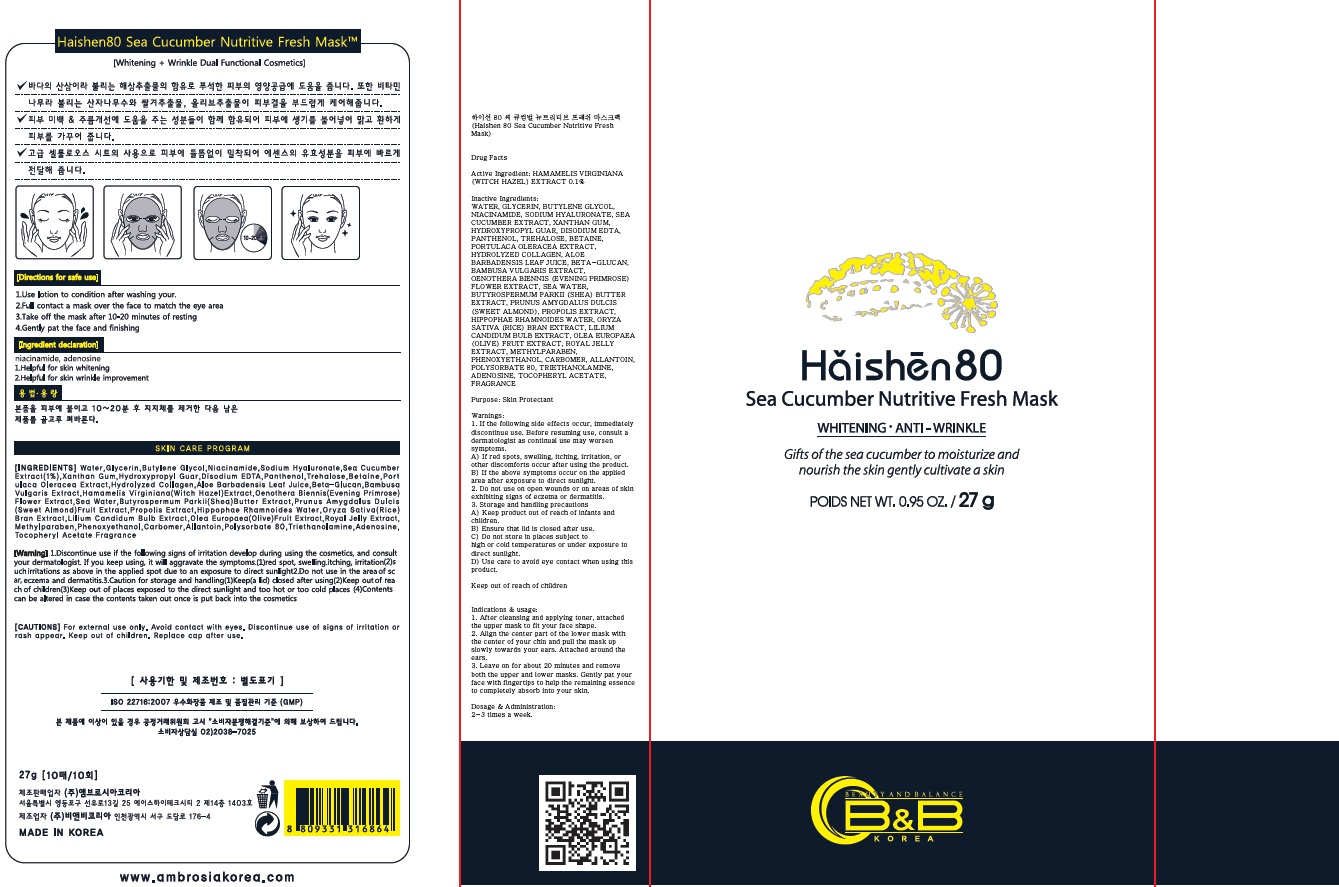 DRUG LABEL: Haishen 80 Sea Cucumber Nutritive Fresh Mask
NDC: 70603-020 | Form: PATCH
Manufacturer: JUNGLEFOOD CO., LTD.
Category: otc | Type: HUMAN OTC DRUG LABEL
Date: 20160408

ACTIVE INGREDIENTS: WITCH HAZEL 0.02 g/27 g
INACTIVE INGREDIENTS: WATER; GLYCERIN

ACTIVE INGREDIENT

Active Ingredient: HAMAMELIS VIRGINIANA (WITCH HAZEL) EXTRACT 0.1%

INACTIVE INGREDIENT

Inactive Ingredients: WATER, GLYCERIN, BUTYLENE GLYCOL, NIACINAMIDE, SODIUM HYALURONATE, SEA CUCUMBER EXTRACT, XANTHAN GUM, HYDROXYPROPYL GUAR, DISODIUM EDTA, PANTHENOL, TREHALOSE, BETAINE, PORTULACA OLERACEA EXTRACT, HYDROLYZED COLLAGEN, ALOE BARBADENSIS LEAF JUICE, BETA-GLUCAN, BAMBUSA VULGARIS EXTRACT, OENOTHERA BIENNIS (EVENING PRIMROSE) FLOWER EXTRACT, SEA WATER, BUTYROSPERMUM PARKII (SHEA) BUTTER EXTRACT, PRUNUS AMYGDALUS DULCIS (SWEET ALMOND), PROPOLIS EXTRACT, HIPPOPHAE RHAMNOIDES WATER, ORYZA SATIVA (RICE) BRAN EXTRACT, LILIUM CANDIDUM BULB EXTRACT, OLEA EUROPAEA (OLIVE) FRUIT EXTRACT, ROYAL JELLY EXTRACT, METHYLPARABEN, PHENOXYETHANOL, CARBOMER, ALLANTOIN, POLYSORBATE 80, TRIETHANOLAMINE, ADENOSINE, TOCOPHERYL ACETATE, FRAGRANCE

PURPOSE

Purpose: Skin Protectant

WARNINGS

Warnings: 1. If the following side effects occur, immediately discontinue use. Before resuming use, consult a dermatologist as continual use may worsen symptoms. A) If red spots, swelling, itching, irritation, or other discomforts occur after using the product. B) If the above symptoms occur on the applied area after exposure to direct sunlight. 2. Do not use on open wounds or on areas of skin exhibiting signs of eczema or dermatitis. 3. Storage and handling precautions A) Keep product out of reach of infants and children. B) Ensure that lid is closed after use. C) Do not store in places subject to high or cold temperatures or under exposure to direct sunlight. D) Use care to avoid eye contact when using this product.

KEEP OUT OF REACH OF CHILDREN

INDICATIONS & USAGE

Indications & usage: 1. After cleansing and applying toner, attached the upper mask to fit your face shape. 2. Align the center part of the lower mask with the center of your chin and pull the mask up slowly towards your ears. Attached around the ears. 3. Leave on for about 20 minutes and remove both the upper and lower masks. Gently pat your face with fingertips to help the remaining essence to completely absorb into your skin.

DOSAGE & ADMINISTRATION

Dosage & Administration: 2-3 times a week.